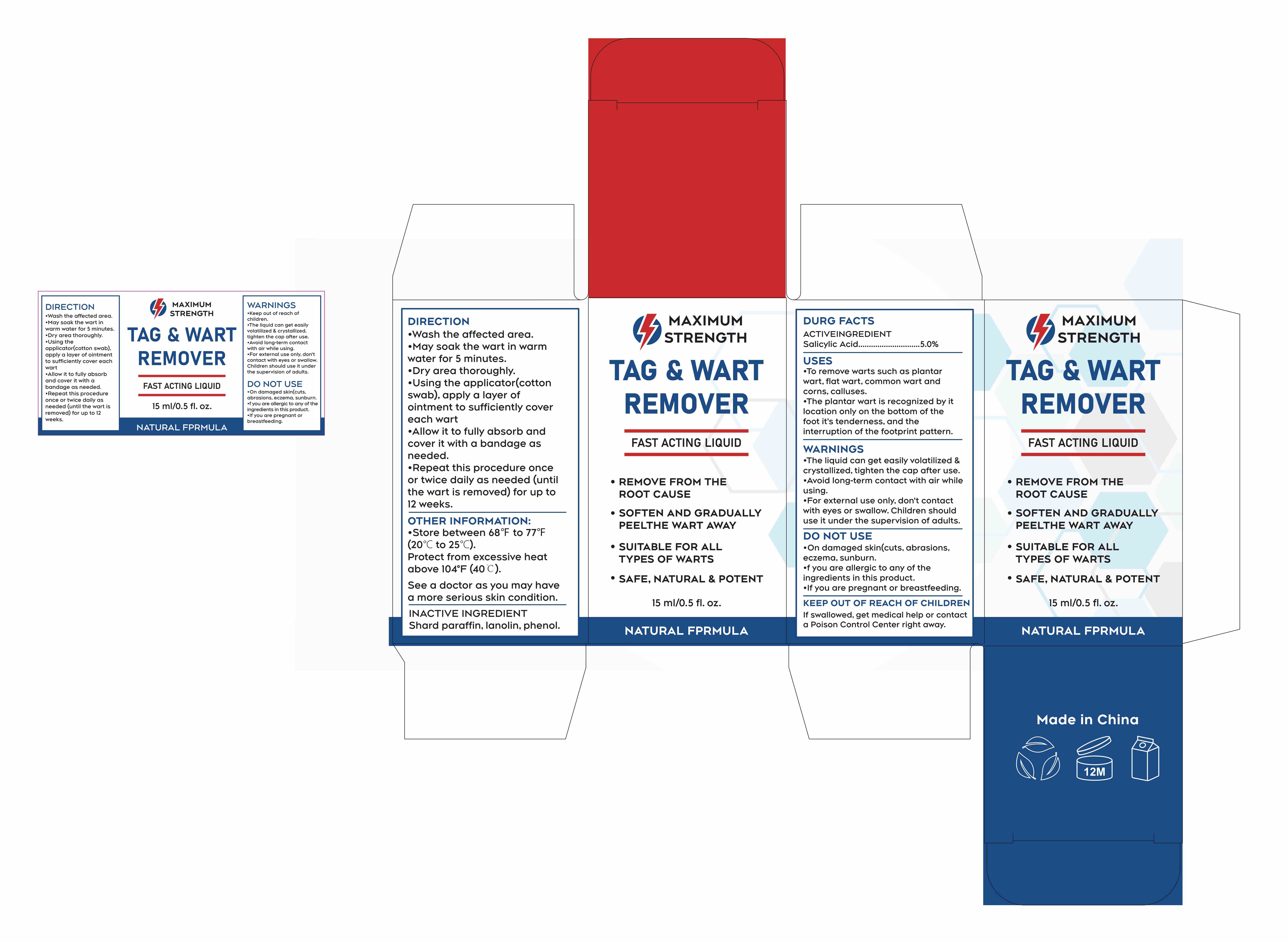 DRUG LABEL: MAXIMUM STRENGTH WART REMOVER
NDC: 84023-113 | Form: LIQUID
Manufacturer: Shenzhen Yangan Technology Co., Ltd.
Category: otc | Type: HUMAN OTC DRUG LABEL
Date: 20241230

ACTIVE INGREDIENTS: SALICYLIC ACID 5 mg/100 mL
INACTIVE INGREDIENTS: LANOLIN; PHENOL

MAXIMUM STRENGTH WART REMOVER LIQUID

ACTIVE INGREDIENT

Salicylic Acid................5.0%

PURPOSE

Wart remover

USES

·To remove warts such as plantar wart, flat wart, common wart and corns, calluses.

·The plantar wart is recognized by it location only on the bottom of the foot it's tenderness, and the interruption of the footprint pattern.

WARNINGS

·The liquid can get easily volatilized & crystallized, tighten the cap after use.

·Avoid long-term contact with air while using.

·For external use only, don't contact with eyes or swallow. Children should use it under the supervision of adults.

DO NOT USE

·On damaged skin(cuts, abrasions, eczema, sunburn.

·If you are allergic to any of the ingredients in this product.

·If you are pregnant or breastfeeding.

KEEP OUT OF REACH OF CHILDREN

·If swallowed, get medical help or contact a Poison Control Center right away.

DOSAGE AND ADMINISTRATION

DIRECTION

·Wash the affected area.

·May soak the wart in warm water for 5 minutes.

·Dry area thoroughly.

·Using the applicator(cotton swab), apply a layer of ointment to sufficiently cover each wart

·Allow it to fully absorb and cover it with a bandage as needed.

·Repeat this procedure once or twice daily as needed (until the wart is removed) for up to 12 weeks.

OTHER INFORMATION:

·Store between 68℉ to 77℉ (20℃ to 25℃).

Protect from excessive heat above 104°F (40℃).

ASK DOCTOR

See a doctor as you may have a more serious skin condition.

INACTIVE INGREDIENT

Shard paraffin, lanolin, phenol.